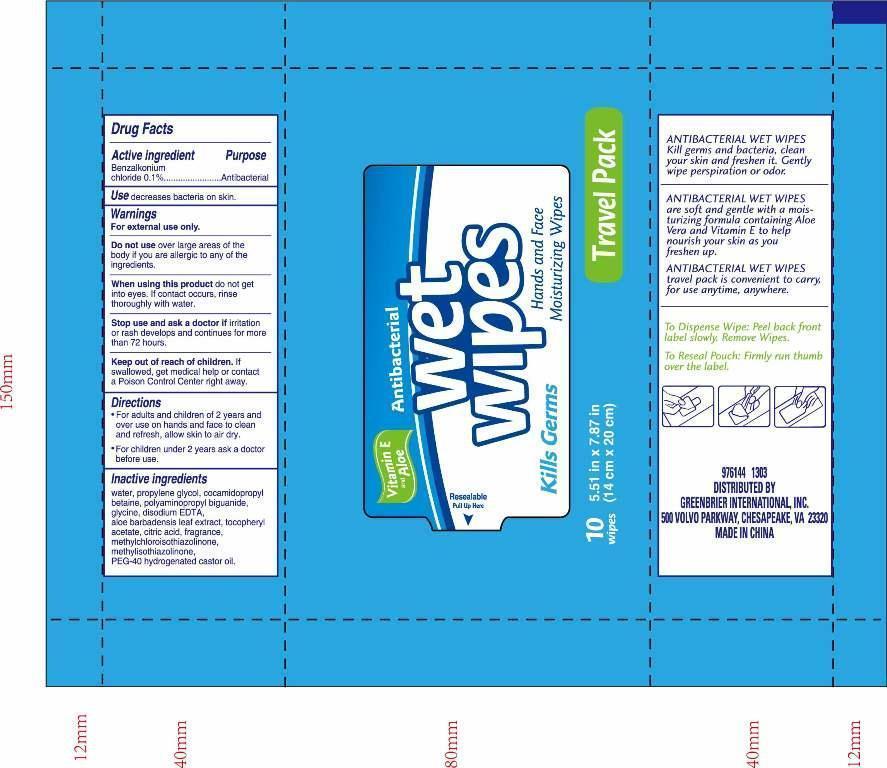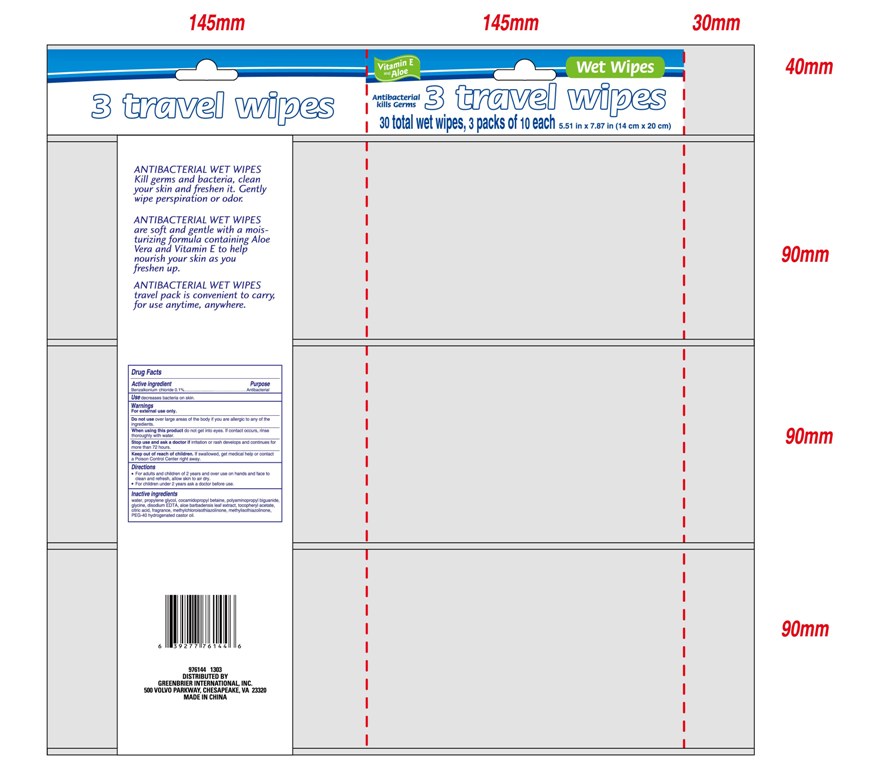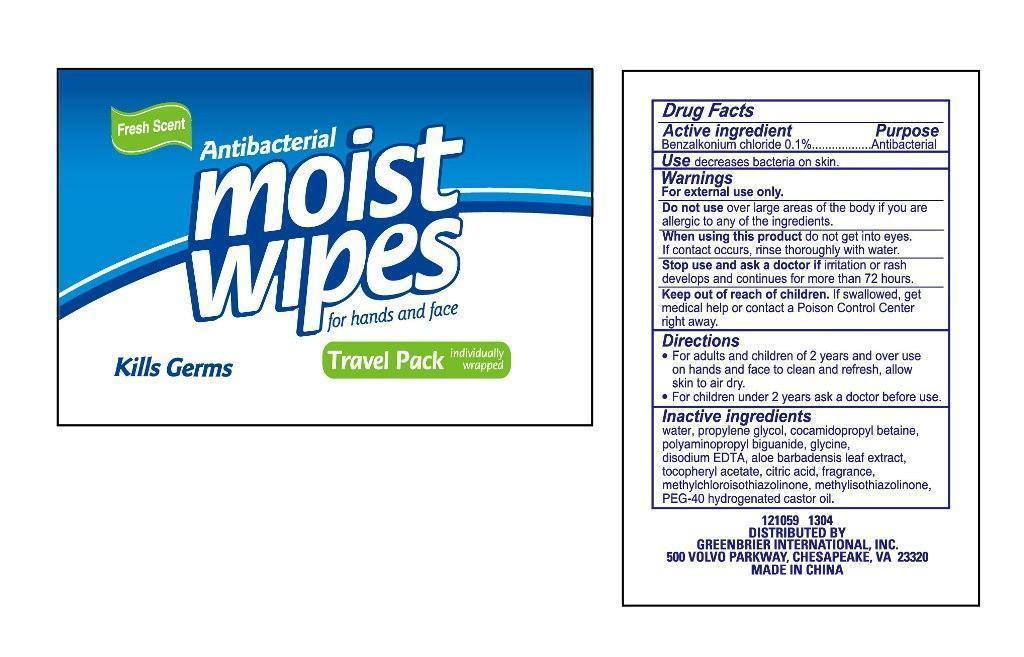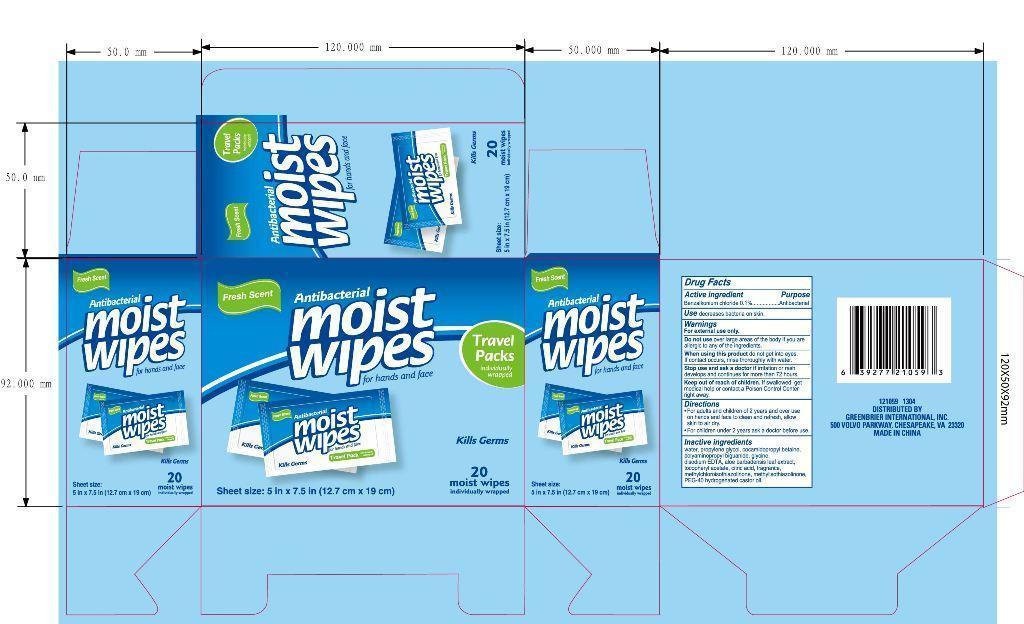 DRUG LABEL: Antibacterial Wet Wipes
NDC: 42255-587 | Form: SWAB
Manufacturer: ZHEJIANG GREENFACE HOUSEWARES CO., LTD.
Category: otc | Type: HUMAN OTC DRUG LABEL
Date: 20180108

ACTIVE INGREDIENTS: BENZALKONIUM CHLORIDE 0.1 g/100 g
INACTIVE INGREDIENTS: WATER; PROPYLENE GLYCOL; COCAMIDOPROPYL BETAINE; POLYAMINOPROPYL BIGUANIDE; GLYCINE; ALOE VERA LEAF; .ALPHA.-TOCOPHEROL ACETATE; CITRIC ACID ACETATE; DISODIUM EDTA-COPPER; METHYLCHLOROISOTHIAZOLINONE; POLYOXYL 40 HYDROGENATED CASTOR OIL

ANTIBACTERIAL WET WIPES 587

Active ingredient

Benzalkonium chloride 0.1%

Purpose

Antibacterial

Use

Use decreases bacteria on skin.

Warnings

For external use only.

Do not use over large areas of the body if you are allergic to any of the ingredients.

When using this product do not get into eyes. If contact occurs, rinse thoroughly with water.

Stop use and ask a doctor if irritation or rash develops and continues for more than 72 hours.

Keep out of reach of children. If swallowed, get medical help or contact a PoisonControlCenterright away.

Keep out of reach of children. If swallowed, get

medical help or contact aPoisonControlCenter

right away.

Directions

For adults and children of 2 years and over use on hands and face to clean and refresh, allow skin to air dry.

For children under 2 years ask a doctor before use.

INACTIVE INGREDIENT

water, propylene glycol, cocamidopropyl betaine, polyaminopropyl biguanide, glycine, disodium EDTA, aloe barbadensis leaf extract, tocopheryl acetate, citric acid, fragrance, methylchloroisothiazolinone, methylisothiazolinone, PEG-40 hydrogenated castor oil.